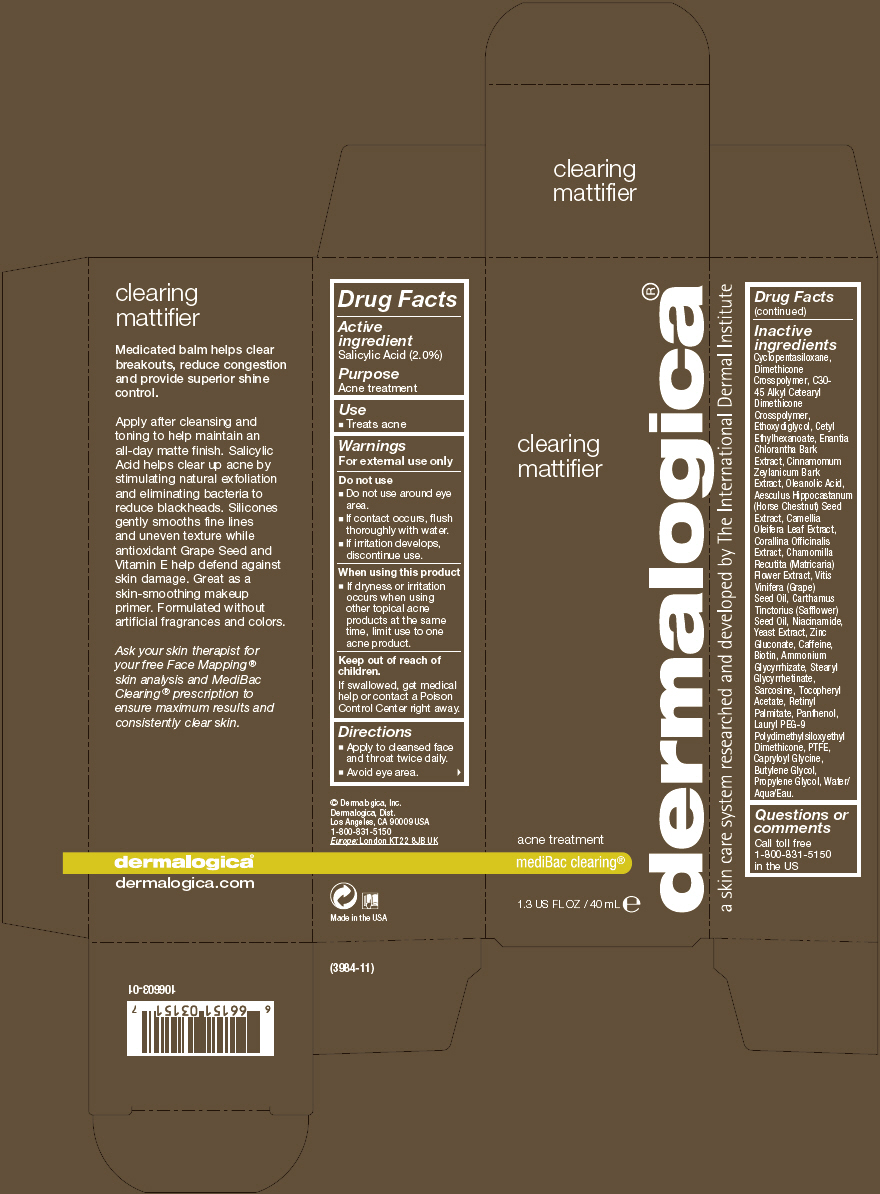 DRUG LABEL: Clearing Mattifier
NDC: 68479-411 | Form: LOTION
Manufacturer: Dermalogica, Inc.
Category: otc | Type: HUMAN OTC DRUG LABEL
Date: 20151120

ACTIVE INGREDIENTS: Salicylic Acid 20 mg/1 mL
INACTIVE INGREDIENTS: Cyclomethicone 5; Diethylene Glycol Monoethyl Ether; Cetyl Ethylhexanoate; Water; Annickia Chlorantha Bark; Cinnamon Bark Oil; Oleanolic Acid; Horse Chestnut; Camellia Oleifera Leaf; Corallina Officinalis; Chamomile; Grape Seed Oil; Safflower Oil; Niacinamide; Yeast, Unspecified; Zinc Gluconate; Caffeine; Biotin; Ammonium Glycyrrhizate; Stearyl Glycyrrhetinate; Sarcosine; .Alpha.-Tocopherol Acetate; Vitamin A Palmitate; Panthenol; Lauryl PEG-9 Polydimethylsiloxyethyl Dimethicone; POLYTETRAFLUOROETHYLENE; Capryloyl Glycine; Butylene Glycol; Propylene Glycol

Clearing Mattifier

Drug Facts

Active ingredient

Salicylic Acid (2.0%)

Purpose

Acne treatment

Use

- Treats acne

Warnings

For external use only

- Do not use around eye area.
- If contact occurs, flush thoroughly with water.
- If irritation develops, discontinue use.

When using this product

- If dryness or irritation occurs when using other topical acne products at the same time, limit use to one acne product.

Keep out of reach of children.

If swallowed, get medical help or contact a Poison Control Center right away.

Directions

- Apply to cleansed face and throat twice daily.
- Avoid eye area.

Inactive ingredients

Cyclopentasiloxane, Dimethicone Crosspolymer, C30-45 Alkyl Cetearyl Dimethicone Crosspolymer, Ethoxydiglycol, Cetyl Ethylhexanoate, Enantia Chlorantha Bark Extract, Cinnamomum Zeylanicum Bark Extract, Oleanolic Acid, Aesculus Hippocastanum (Horse Chestnut) Seed Extract, Camellia Oleifera Leaf Extract, Corallina Officinalis Extract, Chamomilla Recutita (Matricaria) Flower Extract, Vitis Vinifera (Grape) Seed Oil, Carthamus Tinctorius (Safflower) Seed Oil, Niacinamide, Yeast Extract, Zinc Gluconate, Caffeine, Biotin, Ammonium Glycyrrhizate, Stearyl Glycyrrhetinate, Sarcosine, Tocopheryl Acetate, Retinyl Palmitate, Panthenol, Lauryl PEG-9 Polydimethylsiloxyethyl Dimethicone, PTFE, Capryloyl Glycine, Butylene Glycol, Propylene Glycol, Water/Aqua/Eau.

Questions or comments

Call toll free 1-800-831-5150 in the US

PRINCIPAL DISPLAY PANEL - 40 mL Tube Carton

clearing
mattifier

acne treatment

mediBac clearing®

1.3 US FL OZ / 40 mL e

dermalogica®